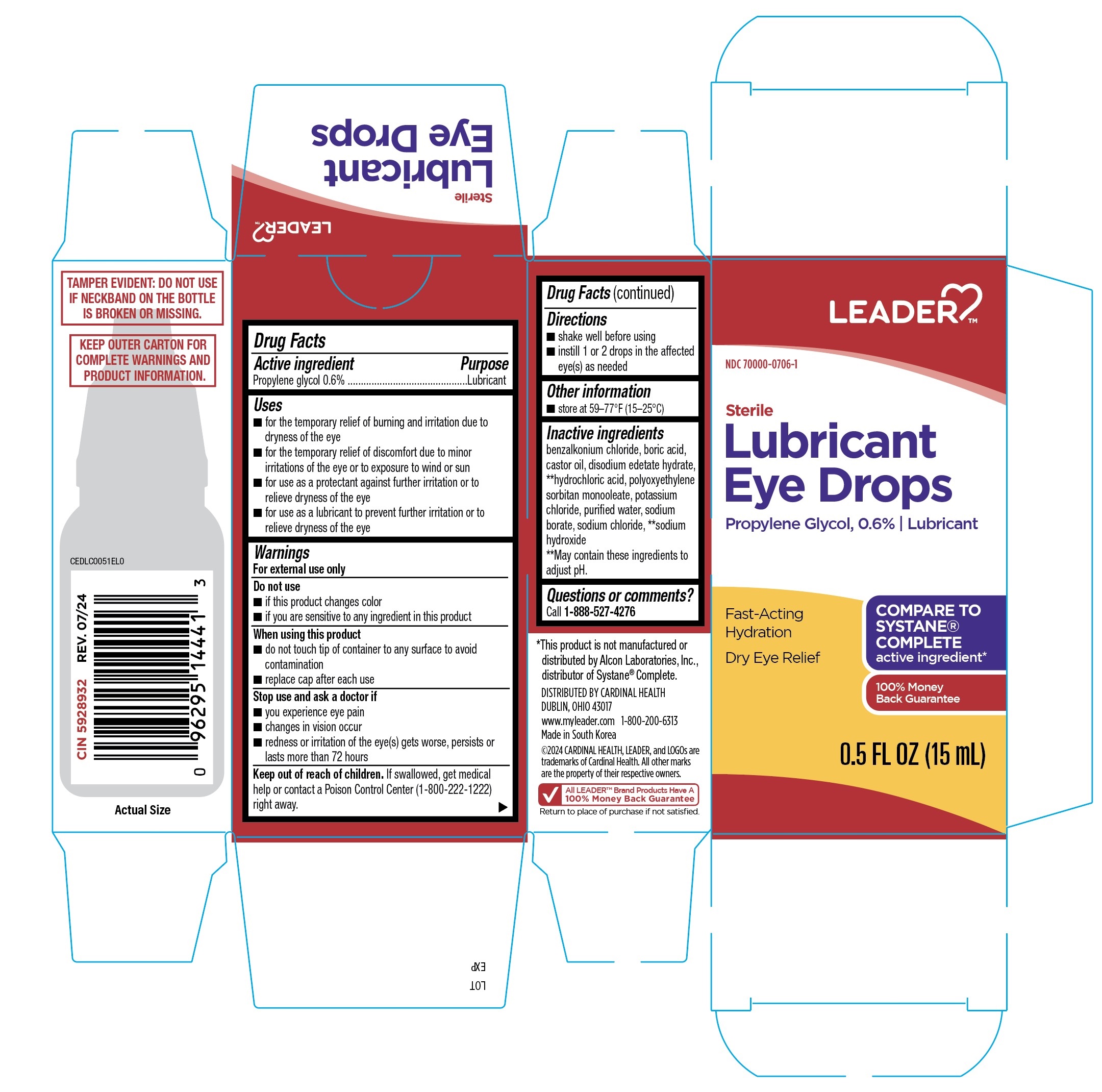 DRUG LABEL: Leader Lubricant Eye Drops Fast-Acting Hydration
NDC: 70000-0706 | Form: SOLUTION/ DROPS
Manufacturer: LEADER/Cardinal Health 110, Inc.
Category: otc | Type: HUMAN OTC DRUG LABEL
Date: 20251230

ACTIVE INGREDIENTS: PROPYLENE GLYCOL 0.6 g/100 mL
INACTIVE INGREDIENTS: PEG-6 SORBITAN OLEATE; HYDROCHLORIC ACID; SODIUM HYDROXIDE; BENZALKONIUM CHLORIDE; BORIC ACID; WATER; SODIUM CHLORIDE; CASTOR OIL; EDETATE DISODIUM; SODIUM BORATE; POTASSIUM CHLORIDE

Leader Lubricant Eye Drops Fast-Acting Hydration 15mL (PLD)

Active ingredient

Propylene glycol 0.6%

Purpose

Lubricant

Uses

- for the temporary relief of burning and irritation due to dryness of the eye
- for the temporary relief of discomfort due to minor irritations of the eye or exposure to wind or sun
- for use as a protectant against further irritation or to relieve dryness of the eye
- for use as a lubricant to prevent further irritation or to relieve dryness of the eye

Warnings

For external use only

Do not use

- if this product changes color
- if you are sensitive to any ingredient in this product

When using this product

- do not touch tip of container to any surface to avoid contamination
- replace cap after each use

Stop use and ask a doctor if

- you experience eye pain
- changes in vision occur
- redness or irritation of the eye(s) gets worse, persists or lasts more than 72 hours

Keep out of reach of children.

If swallowed, get medical help or contact a Poison Control Center (1-800-222-1222) right away.

Directions

- shake well before using
- instill 1 or 2 drops in the affected eye(s) as needed

Other information

store at 59-77ºF (15-25ºC)

Inactive ingredients

benzalkonium chloride, boric acid, castor oil, disodium edetate hydrate, **hydrochloric acid, polyoxyethylene sorbitan monooleate, potassium chloride, purified water, sodium borate, sodium chloride, **sodium hydroxide

**May contain these ingredients to adjust pH.

Questions or comments?

Call 1-888-527-4276